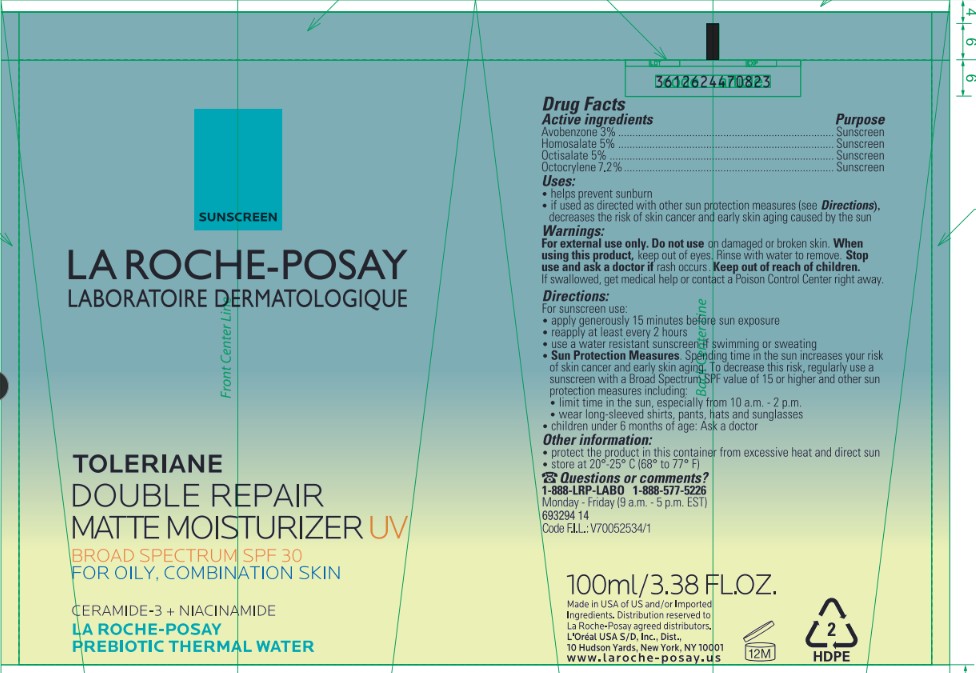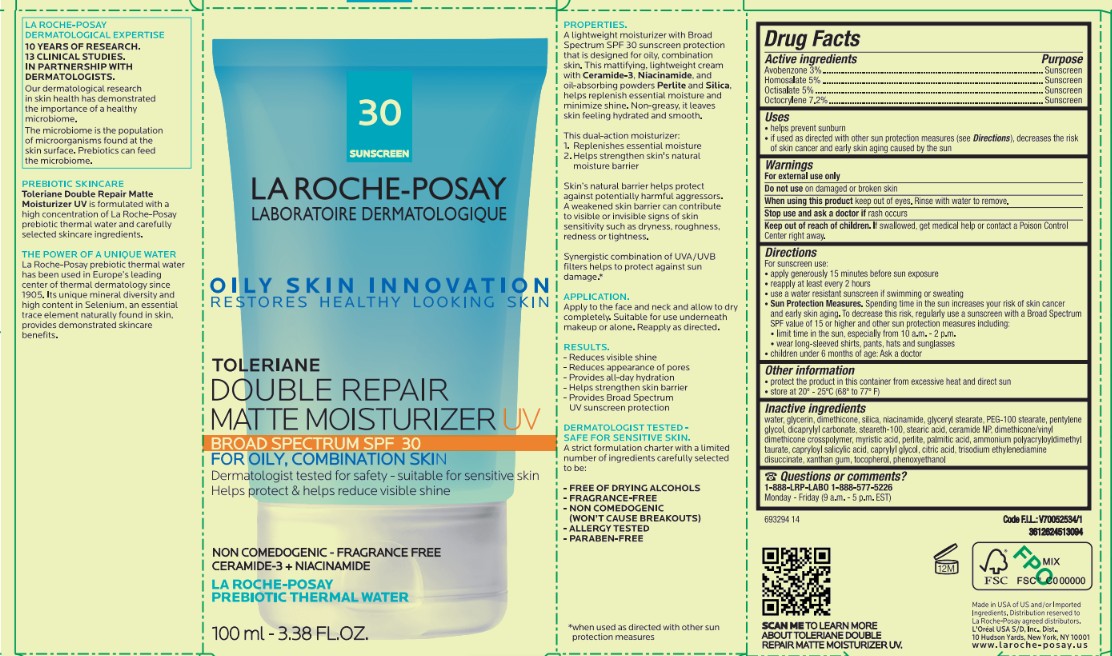 DRUG LABEL: LA ROCHE POSAY LABORATOIRE DERMATOLOGIQUE TOLERAINE DOUBLE REPAIR MATTE MOISTURIZER UV BROAD SPECTRUM SPF 30 FOR OILY, COMBINATION SKIN
NDC: 49967-387 | Form: CREAM
Manufacturer: L’Oreal USA Products Inc
Category: otc | Type: HUMAN OTC DRUG LABEL
Date: 20250630

ACTIVE INGREDIENTS: AVOBENZONE 30 mg/1 mL; HOMOSALATE 50 mg/1 mL; OCTISALATE 50 mg/1 mL; OCTOCRYLENE 72 mg/1 mL
INACTIVE INGREDIENTS: WATER; GLYCERIN; DIMETHICONE; SILICA; NIACINAMIDE; GLYCERYL STEARATE; PEG-100 STEARATE; PENTYLENE GLYCOL; DICAPRYLYL CARBONATE; STEARETH-100; STEARIC ACID; CERAMIDE NP; MYRISTIC ACID; PERLITE; PALMITIC ACID; AMMONIUM POLYACRYLOYLDIMETHYL TAURATE; CAPRYLOYL SALICYLIC ACID; CAPRYLYL GLYCOL; CITRIC ACID; TRISODIUM ETHYLENEDIAMINE DISUCCINATE; XANTHAN GUM; TOCOPHEROL; PHENOXYETHANOL

Drug Facts

Active ingredients

Avobenzone 3%

Homosalate 5%

Octisalate 5%

Octocrylene 7.2%

Purpose

Sunscreen

Uses

- helps prevent sunburn
- if used as directed with other sun protection measures (see Directions), decreases the risk of skin cancer and early skin aging caused by the sun

Warnings

For external use only

Do not use

on damaged or broken skin

When using this product

keep out of eyes. Rinse with water to remove.

Stop use and ask a doctor if

rash occurs.

Keep out of reach of children.

If swallowed, get medical help or contact a Poison Control Center right away.

Directions

For sunscreen use:

- apply generously 15 minutes before sun exposure
- reapply at least every 2 hours
- use a water resistant sunscreen if swimming or sweating
- Sun Protection Measures. Spending time in the sun increases your risk of skin cancer and early skin aging. To decrease this risk, regulary use a sunscreen with a Broad Spectrum SPF value of 15 or higher and other sun protection measures including:
- limit time in the sun, especially from 10 a.m. - 2 p.m.
- wear long-sleeved shirts, pants, hats and sunglasses
- children under 6 months of age: Ask a doctor

Other information

- protect the producct in this container from excessive heat and direct sun
- store at 20°-25°C (68° to 77° F)

Inactive ingredients

water, glycerin, dimethicone, silica, niacinamide, glyceryl stearate, PEG-100 stearate, pentylene glycol, dicaprylyl carbonate, steareth-100, stearic acid, ceramide NP, dimethicone/vinyl dimethicone crosspolymer, myristic acid, perlite, palmitic acid, ammonium polyacryloyldimethyl taurate, capryloyl salicylic acid, caprylyl glycol, citric acid, trisodium ethylenediamine disuccinate, xanthan gum, tocopherol, phenoxyethanol

Questions or Comments?

1-888-LRP-LABO 1-888-577-5226

Monday-Friday (9 a.m.-5 p.m. EST)